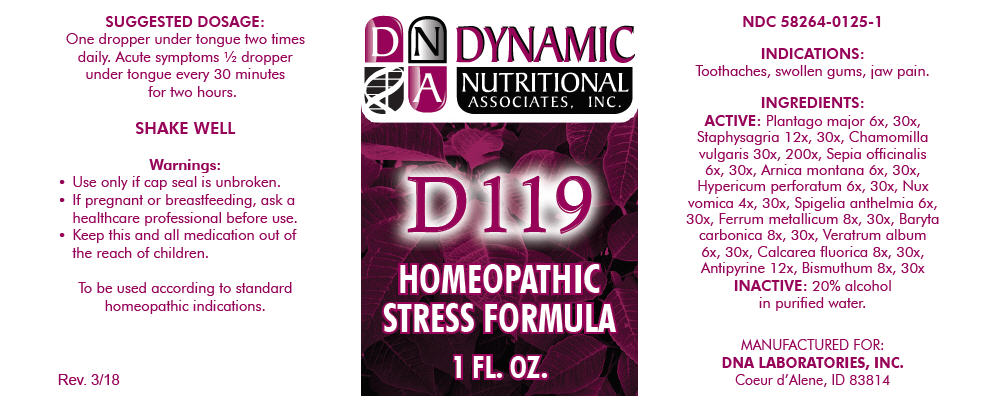 DRUG LABEL: D-119
NDC: 58264-0125 | Form: SOLUTION
Manufacturer: DNA Labs, Inc.
Category: homeopathic | Type: HUMAN OTC DRUG LABEL
Date: 20250113

ACTIVE INGREDIENTS: PLANTAGO MAJOR 6 [hp_X]/1 mL; DELPHINIUM STAPHISAGRIA SEED 12 [hp_X]/1 mL; MATRICARIA CHAMOMILLA 30 [hp_X]/1 mL; SEPIA OFFICINALIS JUICE 6 [hp_X]/1 mL; ARNICA MONTANA 6 [hp_X]/1 mL; HYPERICUM PERFORATUM 6 [hp_X]/1 mL; STRYCHNOS NUX-VOMICA SEED 4 [hp_X]/1 mL; SPIGELIA ANTHELMIA 6 [hp_X]/1 mL; IRON 8 [hp_X]/1 mL; BARIUM CARBONATE 8 [hp_X]/1 mL; VERATRUM ALBUM ROOT 6 [hp_X]/1 mL; CALCIUM FLUORIDE 8 [hp_X]/1 mL; ANTIPYRINE 12 [hp_X]/1 mL; BISMUTH SUBNITRATE 8 [hp_X]/1 mL
INACTIVE INGREDIENTS: ALCOHOL; WATER

D-119

NDC 58264-0125-1

INDICATIONS

PURPOSE

Toothaches, swollen gums, jaw pain.

INGREDIENTS

ACTIVE

Plantago major 6x, 30x, Staphysagria 12x, 30x, Chamomilla vulgaris 30x, 200x, Sepia officinalis 6x, 30x, Arnica montana 6x, 30x, Hypericum perforatum 6x, 30x, Nux vomica 4x, 30x, Spigelia anthelmia 6x, 30x, Ferrum metallicum 8x, 30x, Baryta carbonica 8x, 30x, Veratrum album 6x, 30x, Calcarea fluorica 8x, 30x, Antipyrine 12x, Bismuthum 8x, 30x

INACTIVE

20% alcohol in purified water.

SUGGESTED DOSAGE

One dropper under tongue two times daily. Acute symptoms ½ dropper under tongue every 30 minutes for two hours.

STORAGE AND HANDLING

SHAKE WELL

Warnings

- Use only if cap seal is unbroken.

PREGNANCY OR BREAST FEEDING

- If pregnant or breastfeeding, ask a healthcare professional before use.

KEEP OUT OF REACH OF CHILDREN

- Keep this and all medication out of the reach of children.

To be used according to standard homeopathic indications.

PRINCIPAL DISPLAY PANEL - 1 FL. OZ. Bottle Label

DYNAMIC
NUTRITIONAL
ASSOCIATES, INC.

D 119

HOMEOPATHIC
STRESS FORMULA

1 FL. OZ.